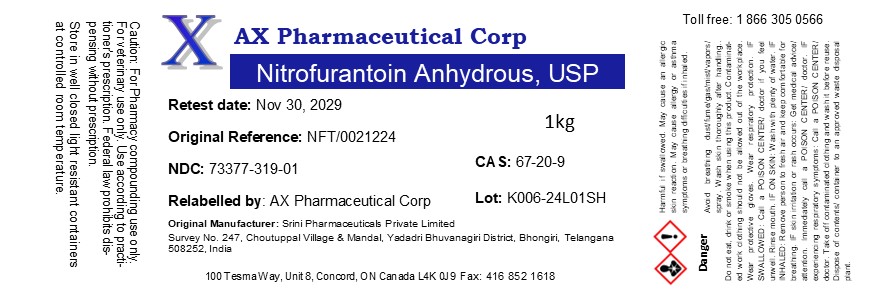 DRUG LABEL: Nitrofurantoin Anhydrous
NDC: 73377-319 | Form: POWDER
Manufacturer: AX Pharmaceutical Corp
Category: other | Type: BULK INGREDIENT - ANIMAL DRUG
Date: 20260119

ACTIVE INGREDIENTS: NITROFURANTOIN 1 g/1 g

Nitrofurantoin Anhydrous